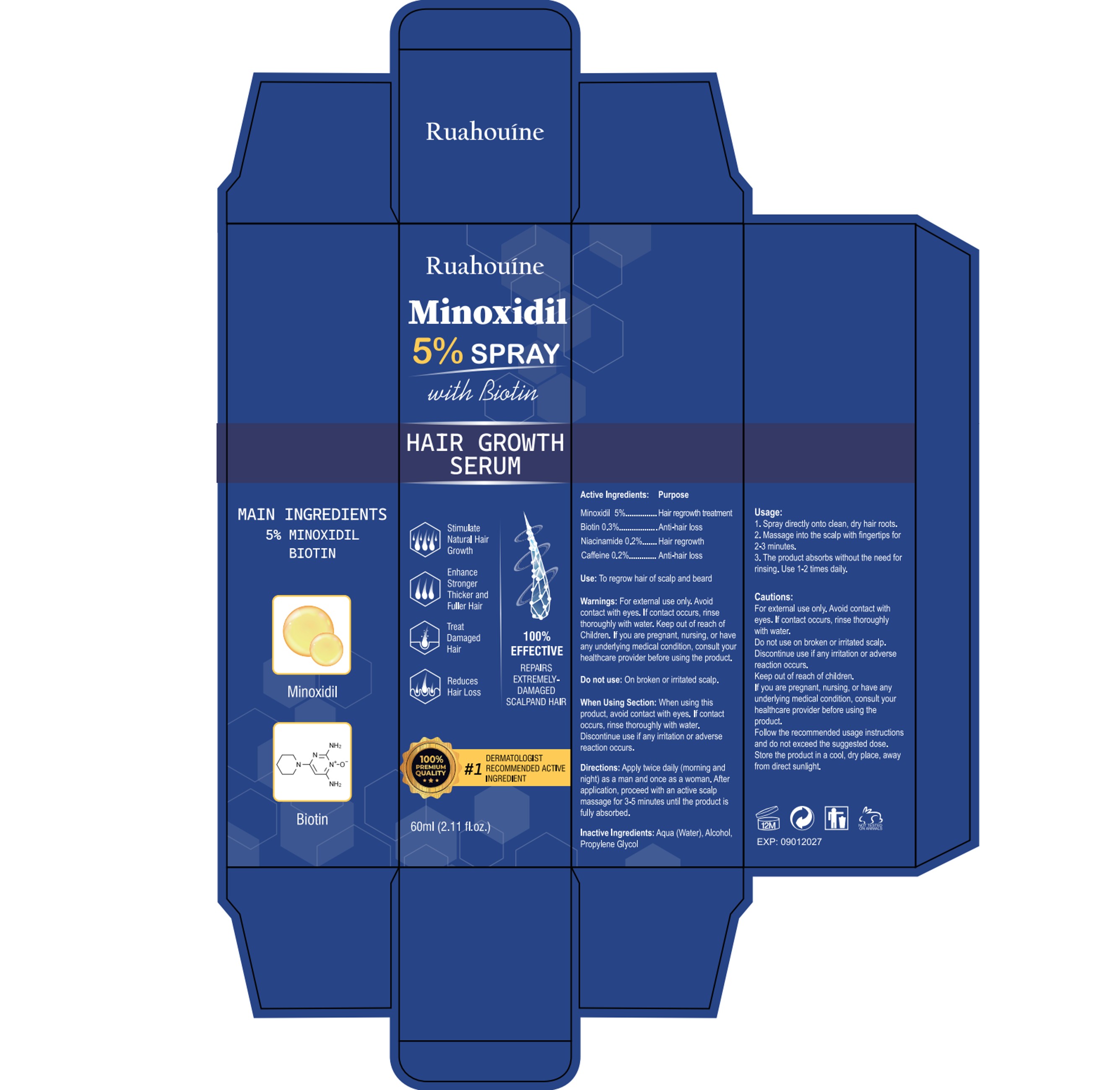 DRUG LABEL: 5%Minoxidil Hair Growth Sprays Serum
NDC: 84355-004 | Form: LIQUID
Manufacturer: Guangzhou Binsi Clothing Co.,Ltd.
Category: otc | Type: HUMAN OTC DRUG LABEL
Date: 20250304

ACTIVE INGREDIENTS: NIACINAMIDE 0.2 g/100 mL; CAFFEINE 0.2 g/100 mL; MINOXIDIL 5 g/100 mL; BIOTIN 0.3 g/100 mL
INACTIVE INGREDIENTS: ALCOHOL; WATER; PROPYLENE GLYCOL

5%Minoxidil Hair Growth Sprays Serum

ACTIVE INGREDIENT

Minoxidil 5%
Biotin 0.3%
Niacinamide 0.2%
Caffeine 0.2%

PURPOSE

Hair regrowth treatment

INDICATIONS AND USAGE

Use: To regrow hair of scalp and beard

WARNINGS

For extemal use only.
Avoidcontact with eyes. lf contact occurs, rinsethoroughly with water.
Keep out of reach ofChildren.
lf you are pregnant, nursing, or haveany underying medical condition, consult yourhealthcare provider before using the produet.

DO NOT USE

On broken or irritated scalp.

WHEN USING

When Using Section: When using thisproduct, avoid contact with eyes. lf contactoccurs, rinse thoroughly with water.

Discontinue use if any iritation or adversereaction occurs.

Discontinue use if any iritation or adversereaction occurs.

Keep out of reach of Children.

DOSAGE AND ADMINISTRATION

Directions: Apply twice daily (morning andnight) as a man and once as a woman. Afterapplication, proceed with an active scalpmassage for 3-5 minutes until the product isfully absorbed.

INACTIVE INGREDIENT

Water
Alcohol
Propylene Glycol